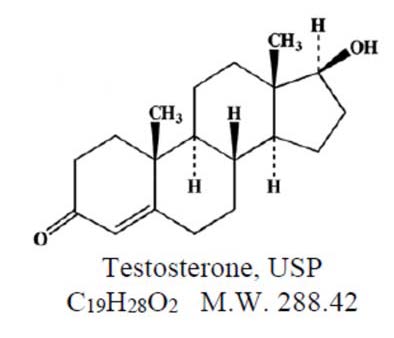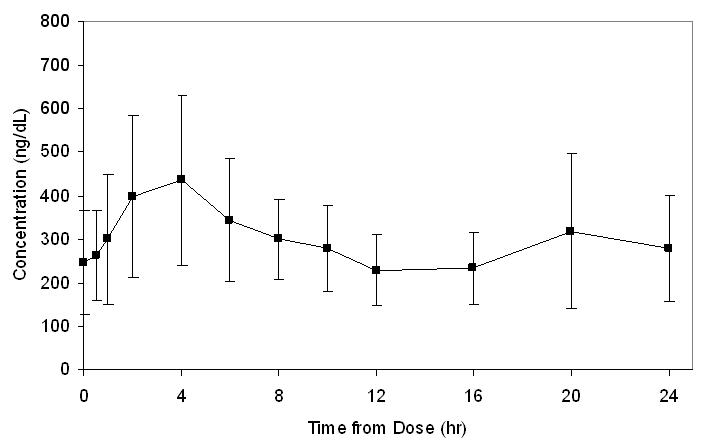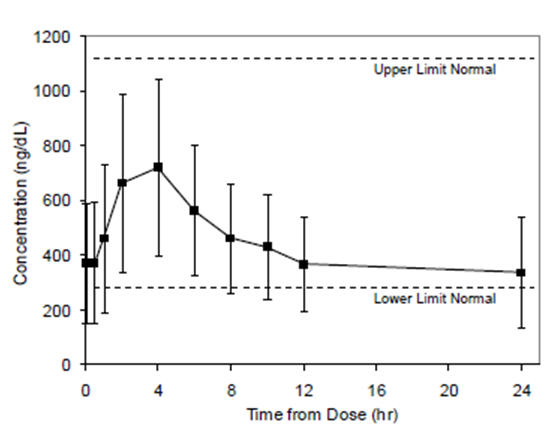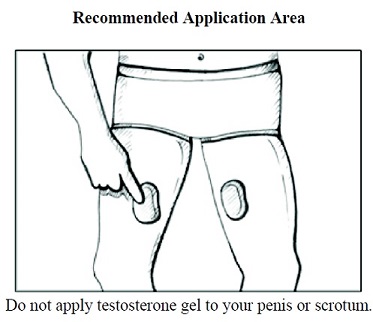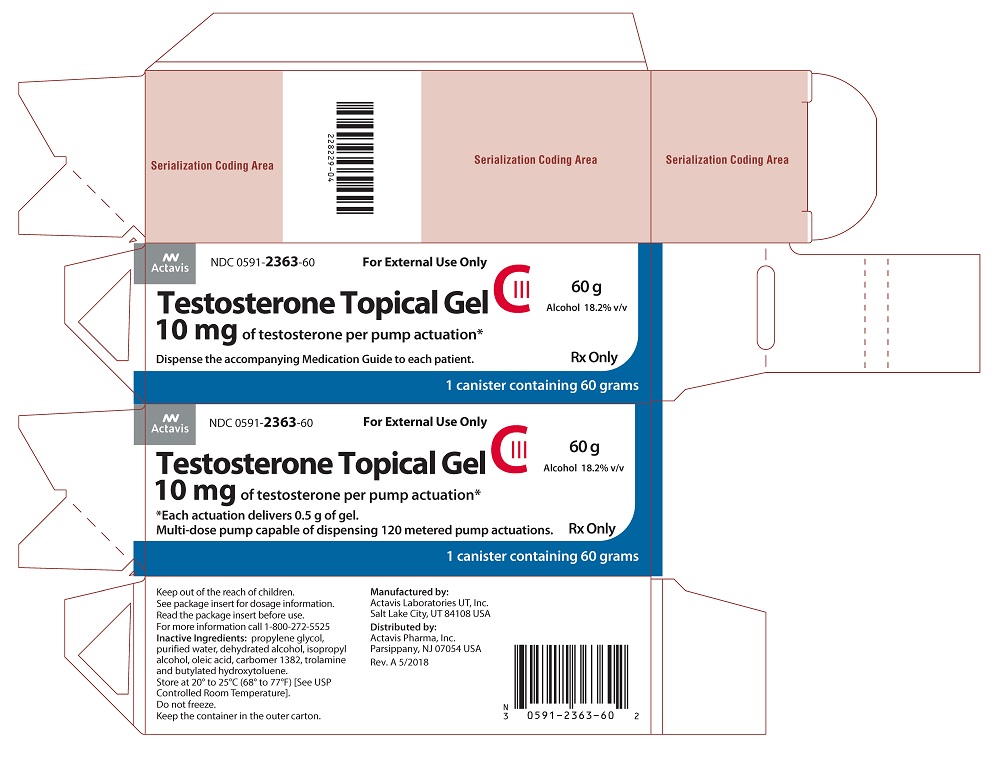 DRUG LABEL: Testosterone
NDC: 0591-2363 | Form: GEL, METERED
Manufacturer: Actavis Pharma, Inc.
Category: prescription | Type: HUMAN PRESCRIPTION DRUG LABEL
Date: 20200601
DEA Schedule: CIII

ACTIVE INGREDIENTS: TESTOSTERONE 10 mg/0.5 g
INACTIVE INGREDIENTS: BUTYLATED HYDROXYTOLUENE; CARBOMER COPOLYMER TYPE C (ALLYL PENTAERYTHRITOL CROSSLINKED); ALCOHOL; ISOPROPYL ALCOHOL; OLEIC ACID; PROPYLENE GLYCOL; WATER; TROLAMINE

HIGHLIGHTS OF PRESCRIBING INFORMATION

These highlights do not include all the information needed to use TESTOSTERONE GEL safely and effectively. See full prescribing information for TESTOSTERONE GEL.
TESTOSTERONE gel, for topical use CIII
Initial U.S. Approval: 1953

RECENT MAJOR CHANGES

Contraindications (4) 03/2020

WARNING: SECONDARY EXPOSURE TO TESTOSTERONE

See full prescribing information for complete boxed warning.

- Virilization has been reported in children who were secondarily exposed to testosterone gel. (5.2, 6.2)
- Children should avoid contact with unwashed or unclothed application sites in men using testosterone gel. (2.2, 5.2)
- Healthcare providers should advise patients to strictly adhere to recommended instructions for use. (2.2, 5.2, 17)

1 INDICATIONS AND USAGE

Testosterone topical gel is an androgen indicated for replacement therapy in males for conditions associated with a deficiency or absence of endogenous testosterone:

- Primary hypogonadism (congenital or acquired). (1)
- Hypogonadotropic hypogonadism (congenital or acquired). (1)

Limitations of Use

- Safety and efficacy of testosterone topical gel in men with “age-related hypogonadism” have not been established. (1)
- Safety and efficacy of testosterone topical gel in males less than 18 years old have not been established. (8.4)

2 DOSAGE AND ADMINISTRATION

- Prior to initiating testosterone gel, confirm the diagnosis of hypogonadism by ensuring that serum testosterone has been measured in the morning on at least two separate days and that these concentrations are below the normal range. (2)
- Starting dose of testosterone gel is 40 mg of testosterone (4 pump actuations) applied topically once daily in the morning. (2.1)
- Apply to clean, dry, intact skin of the thighs. Do not apply testosterone gel to the genitals or other parts of the body. (2.2)
- Dose adjustment: testosterone gel can be dose adjusted between a minimum of 10 mg of testosterone (1 pump actuation) and a maximum of 70 mg of testosterone (7 pump actuations) on the basis of total serum testosterone concentrations 2 hours post testosterone gel application. The dose should be titrated based on the serum testosterone concentration from a single blood draw 2 hours after applying testosterone gel at approximately 14 days and 35 days after starting treatment or following dose adjustment. In addition, serum testosterone concentration should be assessed periodically thereafter. (2.1)
- Patients should wash hands immediately with soap and water after applying testosterone gel and cover the application site with clothing after the gel has dried. Wash the application site thoroughly with soap and water prior to any situation where skin-to-skin contact of the application site with another person is anticipated. (2.2)
- Testosterone gel is not interchangeable with other topical testosterone products. (2.1)

3 DOSAGE FORMS AND STRENGTHS

- Testosterone topical gel is supplied as a metered-dose pump. One pump actuation delivers 10 mg of testosterone. (3)

4 CONTRAINDICATIONS

- Men with carcinoma of the breast or known or suspected prostate cancer. (4, 5.1)
- Women who are pregnant. Testosterone may cause fetal harm. (4, 5.7, 8.1, 8.2)

5 WARNINGS AND PRECAUTIONS

- Monitor patients with benign prostatic hyperplasia (BPH) for worsening of signs and symptoms of BPH. (5.1)
- Avoid unintentional exposure of women or children to testosterone gel. Secondary exposure to testosterone can produce signs of virilization. Testosterone gel should be discontinued until the cause of virilization is identified. (5.2)
- Venous thromboembolism (VTE), including deep vein thrombosis (DVT) and pulmonary embolism (PE) have been reported in patients using testosterone products. Evaluate patients with signs or symptoms consistent with DVT or PE. (5.4)
- Some postmarketing studies have shown an increased risk of myocardial infarction and stroke associated with use of testosterone replacement therapy. (5.5)
- Exogenous administration of androgens may lead to azoospermia. (5.8)
- Edema with or without congestive heart failure (CHF) may be a complication in patients with pre-existing cardiac, renal, or hepatic disease. (5.10)
- Sleep apnea may occur in those with risk factors. (5.12)
- Monitor serum testosterone, prostate specific antigen (PSA), hemoglobin, hematocrit, liver function tests and lipid concentrations periodically. (5.1, 5.3, 5.9, 5.13)
- Testosterone gel is flammable until dry. (5.16)

6 ADVERSE REACTIONS

The most common adverse reaction (incidence greater than or equal to 3%) is skin reactions at the application site (16.1%). (6.1)

To report SUSPECTED ADVERSE REACTIONS, contact Actavis at 1-888-838-2872 or FDA at 1-800-FDA-1088 or www.fda.gov/medwatch.

7 DRUG INTERACTIONS

- Androgens may decrease blood glucose and therefore may decrease insulin requirements in diabetic patients. (7.1)
- Changes in anticoagulant activity may be seen with androgens. More frequent monitoring of International Normalized Ratio (INR) and prothrombin time is recommended. (7.2)
- Use of testosterone with adrenocorticotropic hormone (ACTH) or corticosteroids may result in increased fluid retention. Use with caution, particularly in patients with cardiac, renal or hepatic disease. (7.3)

8 USE IN SPECIFIC POPULATIONS

- There are insufficient long-term safety data in geriatric patients using testosterone gel to assess the potential risks of cardiovascular disease and prostate cancer. (8.5)

FULL PRESCRIBING INFORMATION

RECENT MAJOR CHANGES

Warnings and Precautions (5.6) 10/2016

WARNING: SECONDARY EXPOSURE TO TESTOSTERONE

- Virilization has been reported in children who were secondarily exposed to testosterone gel [see Warnings and Precautions (5.2) and Adverse Reactions (6.2)].
- Children should avoid contact with unwashed or unclothed application sites in men using testosterone gel [see Dosage and Administration (2.2) and Warnings and Precautions (5.2)].
- Healthcare providers should advise patients to strictly adhere to recommended instructions for use [see Dosage and Administration (2.2), Warnings and Precautions (5.2), and Patient Counseling Information (17)].

1 INDICATIONS AND USAGE

Testosterone topical gel is indicated for replacement therapy in males for conditions associated with a deficiency or absence of endogenous testosterone:

- Primary hypogonadism (congenital or acquired) – testicular failure due to conditions such as cryptorchidism, bilateral torsion, orchitis, vanishing testis syndrome, orchiectomy, Klinefelter’s syndrome, chemotherapy, or toxic damage from alcohol, heavy metals. These men usually have low serum testosterone concentrations and gonadotropins (follicle stimulating hormone [FSH] and luteinizing hormone [LH]) above the normal range.
- Hypogonadotropic hypogonadism (congenital or acquired) – gonadotropin or luteinizing hormone-releasing hormone (LHRH) deficiency or pituitary-hypothalamic injury from tumors, trauma, or radiation. These men have low serum testosterone concentrations but have gonadotropins in the normal or low range.

Limitations of Use

- Safety and efficacy of testosterone topical gel in men with “age-related hypogonadism” (also referred to as “late-onset hypogonadism”) have not been established.
- Safety and efficacy of testosterone topical gel in males less than 18 years old have not been established [see Use in Specific Populations (8.4)].

2 DOSAGE AND ADMINISTRATION

Prior to initiating testosterone gel, confirm the diagnosis of hypogonadism by ensuring that serum testosterone concentrations have been measured in the morning on at least 2 separate days and that these serum testosterone concentrations are below the normal range.

2.1 Dosing and Dose Adjustment

The recommended starting dose of testosterone gel is 40 mg of testosterone (4 pump actuations) applied once daily to the thighs in the morning. The dose can be adjusted between a minimum of 10 mg of testosterone and a maximum of 70 mg of testosterone. To ensure proper dosing, the dose should be titrated based on the serum testosterone concentration from a single blood draw 2 hours after applying testosterone gel at approximately 14 days and 35 days after starting treatment or following dose adjustment. In addition, serum testosterone concentration should be assessed periodically thereafter. Table 1 describes the dose adjustments required at each titration step.

Table 1: Dose Adjustment Criteria
Total Serum Testosterone Concentration 2 hours Post Testosterone Gel Application | Dose Titration
Equal to or greater than 2,500 ng/dL | Decrease daily dose by 20 mg (2 pump actuations)
Equal to or greater than 1,250 and less than 2,500 ng/dL | Decrease daily dose by 10 mg (1 pump actuation)
Equal to or greater than 500 and less than 1,250 ng/dL | No change: continue on current dose
Less than 500 ng/dL | Increase daily dose by 10 mg (1 pump actuation)

The application site and dose of testosterone gel are not interchangeable with other topical testosterone products.

2.2 Administration Instructions

Testosterone gel should be applied directly to clean, dry, intact skin of the front and inner thighs. Do not apply testosterone gel to the genitals or other parts of the body. Patients should be instructed to use one finger to gently rub testosterone gel evenly onto the front and inner area of each thigh as directed in Table 2.

Table 2: Application of Testosterone Gel
Total Dose of | Total Pump | Pump Actuations per Thigh
Testosterone | Actuations | Thigh #1 | Thigh #2
10 mg | 1 | 1 | 0
20 mg | 2 | 1 | 1
30 mg | 3 | 2 | 1
40 mg | 4 | 2 | 2
50 mg | 5 | 3 | 2
60 mg | 6 | 3 | 3
70 mg | 7 | 4 | 3

Once the application site is dry, the site should be covered with clothing [see Clinical Pharmacology (12.3)]. Wash hands thoroughly with soap and water. Avoid applying the gel to the thigh adjacent to the scrotum. Avoid fire, flames, or smoking until the gel has dried since alcohol based products, including testosterone gel, are flammable.

The patient should avoid swimming or showering or washing the administration site for a minimum of 2 hours after application [see Clinical Pharmacology (12.3)].

To obtain a full first dose, it is necessary to prime the canister pump. To do so, with the canister in the upright position, slowly and fully depress the actuator eight times. The first 3 actuations may result in no discharge of gel. Safely discard the gel from the first 8 actuations. It is only necessary to prime the pump before the first dose.

Strict adherence to the following precautions is advised in order to minimize the potential for secondary exposure to testosterone from testosterone gel-treated skin:

- Children and women should avoid contact with unwashed or unclothed application site(s) of men using testosterone gel.
- Testosterone gel should only be applied to the front and inner thighs (area of application should be limited to the area that will be covered by the patient’s shorts or pants).
- Patients should wash their hands immediately with soap and water after applying testosterone gel.
- Patients should cover the application site(s) with clothing (e.g., shorts of sufficient length or pants) after the gel has dried.
- Prior to any situation in which skin-to-skin contact with the application site is anticipated, patients should wash the application site(s) thoroughly with soap and water to remove any testosterone residue.
- In the event that unwashed or unclothed skin to which testosterone gel has been applied comes in direct contact with the skin of another person, the general area of contact on the other person should be washed with soap and water as soon as possible.

3 DOSAGE FORMS AND STRENGTHS

Testosterone gel for topical use only, is supplied in a metered-dose pump. One (1) pump actuation delivers 10 mg of testosterone.

4 CONTRAINDICATIONS

- Testosterone gel is contraindicated in men with carcinoma of the breast or known or suspected carcinoma of the prostate [see Warnings and Precautions (5.1) and Adverse Reactions (6.1)].
- Testosterone gel is contraindicated in women who are pregnant. Testosterone can cause virilization of the female fetus when administered to a pregnant woman [see Use in Specific Populations (8.1, 8.2)].

5 WARNINGS AND PRECAUTIONS

5.1 Worsening of Benign Prostatic Hyperplasia (BPH) and Potential Risk of Prostate Cancer

- Patients with BPH treated with androgens are at an increased risk of worsening of signs and symptoms of BPH. Monitor patients with BPH for worsening signs and symptoms.
- Patients treated with androgens may be at increased risk for prostate cancer. Evaluation of the patients for the presence of prostate cancer prior to initiating and during treatment with androgens is appropriate [see Contraindications (4)].

5.2 Potential for Secondary Exposure to Testosterone

Cases of secondary exposure resulting in virilization of children have been reported in postmarketing surveillance of testosterone gel products. Signs and symptoms have included enlargement of the penis or clitoris, development of pubic hair, increased erections and libido, aggressive behavior, and advanced bone age. In most cases, these signs and symptoms regressed with removal of the exposure to testosterone gel. In a few cases, however, enlarged genitalia did not fully return to age-appropriate normal size, and bone age remained modestly greater than chronological age. The risk of transfer was increased in some of these cases by not adhering to precautions for the appropriate use of the topical testosterone product. Children and women should avoid contact with unwashed or unclothed application sites in men using testosterone gel [see Dosage and Administration (2.2), Use in Specific Populations (8.1), and Clinical Pharmacology (12.3)].

Inappropriate changes in genital size or development of pubic hair or libido in children, or changes in body hair distribution, significant increase in acne, or other signs of virilization in adult women should be brought to the attention of a physician and the possibility of secondary exposure to testosterone gel should also be brought to the attention of a physician. Testosterone gel should be promptly discontinued until the cause of virilization has been identified.

5.3 Polycythemia

Increases in hematocrit, reflective of increases in red blood cell mass, may require lowering or discontinuation of testosterone. Check hematocrit prior to initiating treatment. It would also be appropriate to re-evaluate the hematocrit 3 to 6 months after starting treatment, and then annually. If hematocrit becomes elevated, stop therapy until hematocrit decreases to an acceptable concentration. An increase in red blood cell mass may increase the risk of thromboembolic events.

5.4 Venous Thromboembolism (VTE)

There have been postmarketing reports of venous thromboembolic events, including deep vein thrombosis (DVT) and pulmonary embolism (PE), in patients using testosterone products, such as testosterone gel. Evaluate patients who report symptoms of pain, edema, warmth and erythema in the lower extremity for DVT and those who present with acute shortness of breath for PE. If a venous thromboembolic event is suspected, discontinue treatment with testosterone gel and initiate appropriate workup and management.

5.5 Cardiovascular Risk

Long-term clinical safety trials have not been conducted to assess the cardiovascular outcomes of testosterone replacement therapy in men. To date, epidemiologic studies and randomized controlled trials have been inconclusive for determining the risk of major adverse cardiovascular events (MACE), such as non-fatal myocardial infarction, non-fatal stroke, and cardiovascular death, with the use of testosterone compared to non-use. Some studies, but not all, have reported an increased risk of MACE in association with use of testosterone replacement therapy in men. Patients should be informed of this possible risk when deciding whether to use or to continue to use testosterone gel.

5.6 Abuse of Testosterone and Monitoring of Serum Testosterone Concentrations

Testosterone has been subject to abuse, typically at doses higher than recommended for the approved indication and in combination with other anabolic androgenic steroids. Anabolic androgenic steroid abuse can lead to serious cardiovascular and psychiatric adverse reactions [see Drug Abuse and Dependence (9)].

If testosterone abuse is suspected, check serum testosterone concentrations to ensure they are within therapeutic range. However, testosterone levels may be in the normal or subnormal range in men abusing synthetic testosterone derivatives. Counsel patients concerning the serious adverse reactions associated with abuse of testosterone and anabolic androgenic steroids. Conversely, consider the possibility of testosterone and anabolic androgenic steroid abuse in suspected patients who present with serious cardiovascular or psychiatric adverse events.

5.7 Use in Women

Due to the lack of controlled evaluations in women and potential virilizing effects, testosterone gel is not indicated for use in women [see Contraindications (4) and Use in Specific Populations (8.1, 8.2)].

5.8 Potential for Adverse Effects on Spermatogenesis

With large doses of exogenous androgens, including testosterone gel, spermatogenesis may be suppressed through feedback inhibition of pituitary FSH which could possibly lead to adverse effects on semen parameters including sperm count.

5.9 Hepatic Adverse Effects

Prolonged use of high doses of orally active 17-alpha-alkyl androgens (e.g. methyltestosterone) has been associated with serious hepatic adverse effects (peliosis hepatis, hepatic neoplasms, cholestatic hepatitis, and jaundice). Peliosis hepatis can be a life-threatening or fatal complication. Long-term therapy with testosterone enanthate has produced multiple hepatic adenomas. Testosterone gel is not known to cause these adverse effects.

5.10 Edema

Androgens, including testosterone gel, may promote retention of sodium and water. Edema, with or without congestive heart failure, may be a serious complication in patients with preexisting cardiac, renal, or hepatic disease [see Adverse Reactions (6.2)].

5.11 Gynecomastia

Gynecomastia may develop and persist in patients being treated with androgens, including testosterone gel, for hypogonadism.

5.12 Sleep Apnea

The treatment of hypogonadal men with testosterone may potentiate sleep apnea in some patients, especially those with risk factors such as obesity or chronic lung diseases.

5.13 Lipids

Changes in serum lipid profile may require dose adjustment or discontinuation of testosterone therapy.

5.14 Hypercalcemia

Androgens, including testosterone gel, should be used with caution in cancer patients at risk of hypercalcemia (and associated hypercalciuria). Regular monitoring of serum calcium concentrations is recommended in these patients.

5.15 Decreased Thyroxine-binding Globulin

Androgens, including testosterone gel, may decrease concentrations of thyroxin-binding globulins, resulting in decreased total T4 serum concentrations and increased resin uptake of T3 and T4. Free thyroid hormone concentrations remain unchanged, however, and there is no clinical evidence of thyroid dysfunction.

5.16 Flammability

Alcohol based products, including testosterone gel, are flammable; therefore, patients should be advised to avoid smoking, fire, or flame until the testosterone gel has dried.

6 ADVERSE REACTIONS

6.1 Clinical Trial Experience

Because clinical trials are conducted under widely varying conditions, adverse reaction rates observed in the clinical trials of a drug cannot be directly compared to rates in the clinical trials of another drug and may not reflect the rates observed in clinical practice.

In a controlled multicenter, open-label, non-comparative 90-day clinical study, 149 hypogonadal patients were treated with testosterone gel [see Clinical Studies (14.1)]. Adverse reactions occurred in 22.8% (34/149) of patients. The most common adverse reaction reported in this study was skin reactions associated with the site of application (16.1%; 24/149) of which 79% (19/24) were mild and the remainder were moderate (21%; 5/24) (Table 3).

Table 3: Adverse Reactions Reported in >1% of Patients in the US Phase 3 Clinical Trial of Testosterone Gel
Adverse Reaction | Number (%) of Patients N = 149
Skin reaction | 24 (16.1%)
Prostatic specific antigen increased | 2 (1.3%)
Abnormal dreams | 2 (1.3%)

During the 90-day trial 5 patients (3.4%) discontinued treatment because of adverse reactions. These reactions were: 1 patient with contact dermatitis (considered probably related to testosterone gel application), 1 with application site reaction (considered probably related to testosterone gel application), 1 with gastrointestinal hypomotility (considered possibly related to testosterone gel application), 1 with severe dyspnea (considered not related to testosterone gel application), and 1 with moderate contusion (considered not related to testosterone gel application).

6.2 Postmarketing Experience

The following adverse reactions have been identified during post approval use of testosterone gel. Because these reactions are reported voluntarily from a population of uncertain size, it is not always possible to reliably estimate their frequency or establish a causal relationship to drug exposure (Table 4).

Table 4: Adverse Drug Reactions from Post Approval Experience of Testosterone Gel by System Organ Class
System Organ Class | Adverse Reaction
Blood and lymphatic system disorders | Polycythemia
Eye disorders | Vitreous detachment
Gastrointestinal disorders | Abdominal symptoms
General disorders and administrative site conditions | Application site erythema, irritation, pruritus, and swelling; fatigue, influenza like illness, and malaise
Investigations | Decreased serum testosterone, increased hematocrit and hemoglobin
Musculoskeletal and connective tissue disorders | Pain in extremity
Nervous system disorders | Dizziness, headache, and migraine
Reproductive system and breast disorders | Erectile dysfunction and priapism
Skin and subcutaneous tissue disorders | Allergic dermatitis, erythema, rash, and papular rash
Vascular disorders | Venous thromboembolism
Cardiovascular disorders | Myocardial infarction and stroke

Secondary Exposure to Testosterone in Children
Cases of secondary exposure to testosterone resulting in virilization of children have been reported in postmarketing surveillance of testosterone gel products. Signs and symptoms of these reported cases have included enlargement of the clitoris (with surgical intervention) or the penis, development of pubic hair, increased erections and libido, aggressive behavior, and advanced bone age. In most cases with a reported outcome, these signs and symptoms were reported to have regressed with removal of the testosterone gel exposure. In a few cases, however, enlarged genitalia did not fully return to age appropriate normal size, and bone age remained modestly greater than chronological age. In some of the cases, direct contact with the sites of application on the skin of men using testosterone gel was reported. In at least 1 reported case, the reporter considered the possibility of secondary exposure from items such as the testosterone gel user’s shirts and/or other fabric, such as towels and sheets [see Warnings and Precautions (5.2)].

7 DRUG INTERACTIONS

7.1 Insulin

Changes in insulin sensitivity or glycemic control may occur in patients treated with androgens. In diabetic patients, the metabolic effects of androgens may decrease blood glucose and, therefore, may decrease insulin requirements.

7.2 Oral Anticoagulants

Changes in anticoagulant activity may be seen with androgens, therefore more frequent monitoring of international normalized ratio (INR) and prothrombin time are recommended in patients taking anticoagulants, especially at the initiation and termination of androgen therapy.

7.3 Corticosteroids

The concurrent administration of testosterone with adrenocorticotropic hormone (ACTH) or corticosteroids may result in increased fluid retention and requires careful monitoring particularly in patients with cardiac, renal, or hepatic disease.

8 USE IN SPECIFIC POPULATIONS

8.1 Pregnancy

Risk Summary

Testosterone gel is contraindicated in pregnant women. Testosterone is teratogenic and may cause fetal harm based on data from animal studies and its mechanism of action [see Contraindications (4) and Clinical Pharmacology (12.1)]. Exposure of a female fetus to androgens may result in varying degrees of virilization. In animal developmental studies, exposure to testosterone in utero resulted in hormonal and behavioral changes in offspring and structural impairments of reproductive tissues in female and male offspring. These studies did not meet current standards for nonclinical development toxicity studies.

Data

Animal Data

In developmental studies conducted in rats, rabbits, pigs, sheep, and rhesus monkeys, pregnant animals received intramuscular injection of testosterone during the period of organogenesis. Testosterone treatment at doses that were comparable to those used for testosterone replacement therapy resulted in structural impairments in both female and male offspring. Structural impairments observed in females included increased anogenital distance, phallus development, empty scrotum, no external vagina, intrauterine growth retardation, reduced ovarian reserve, and increased ovarian follicular recruitment. Structural impairments seen in male offspring included increased testicular weight, larger seminal tubular lumen diameter, and higher frequency of occluded tubule lumen. Increased pituitary weight was seen in both sexes.

Testosterone exposure in utero also resulted in hormonal and behavioral changes in offspring. Hypertension was observed in pregnant female rats and their offspring exposed to doses approximately twice those used for testosterone replacement therapy.

8.2 Lactation

Risk Summary

Testosterone gel is not indicated for use in females.

8.3 Females and Males of Reproductive Potential

Infertility

During treatment with large doses of exogenous androgens, including Testosterone gel, spermatogenesis may be suppressed through feedback inhibition of the hypothalamic-pituitary-testicular axis [see Warnings and Precautions (5.8)], possibly leading to adverse effects on semen parameters including sperm count. Reduced fertility is observed in some men taking testosterone replacement therapy. Testicular atrophy, subfertility, and infertility have also been reported in men who abuse anabolic androgenic steroids [see Drug Abuse and Dependence (9.2)]. With either type of use, the impact on fertility may be irreversible.

8.4 Pediatric Use

The safety and efficacy of testosterone gel in pediatric patients less than 18 years old has not been established. Improper use may result in acceleration of bone age and premature closure of epiphyses.

8.5 Geriatric Use

There have not been sufficient numbers of geriatric patients involved in controlled clinical studies utilizing testosterone gel to determine whether efficacy in those over 65 years of age differs from younger subjects. Of the 149 patients enrolled in the pivotal clinical study utilizing testosterone gel, 20 were over 65 years of age. Additionally, there are insufficient long-term safety data in geriatric patients to assess the potential risks of cardiovascular disease and prostate cancer.

Geriatric patients treated with androgens may also be at risk for worsening of signs and symptoms of BPH.

8.6 Renal Impairment

No studies were conducted in patients with renal impairment.

8.7 Hepatic Impairment

No studies were conducted in patients with hepatic impairment.

9 DRUG ABUSE AND DEPENDENCE

9.1 Controlled Substance

Testosterone gel contains testosterone, a Schedule III controlled substance in the Controlled Substances Act.

9.2 Abuse

Drug abuse is intentional non-therapeutic use of a drug, even once, for its rewarding psychological and physiological effects. Abuse and misuse of testosterone are seen in male and female adults and adolescents. Testosterone, often in combination with other anabolic androgenic steroids (AAS), and not obtained by prescription through a pharmacy, may be abused by athletes and bodybuilders. There have been reports of misuse of men taking higher doses of legally obtained testosterone than prescribed and continuing testosterone despite adverse events or against medical advice.

Abuse-Related Adverse Reactions

Serious adverse reactions have been reported in individuals who abuse anabolic androgenic steroids, and include cardiac arrest, myocardial infarction, hypertrophic cardiomyopathy, congestive heart failure, cerebrovascular accident, hepatotoxicity, and serious psychiatric manifestations, including major depression, mania, paranoia, psychosis, delusions, hallucinations, hostility, and aggression.

The following adverse reactions have also been reported in men: transient ischemic attacks, convulsions, hypomania, irritability, dyslipidemias, testicular atrophy, subfertility, and infertility.

The following additional adverse reactions have been reported in women: hirsutism, virilization, deepening of voice, clitoral enlargement, breast atrophy, male-pattern baldness, and menstrual irregularities.

The following adverse reactions have been reported in male and female adolescents: premature closure of bony epiphyses with termination of growth, and precocious puberty.

Because these reactions are reported voluntarily from a population of uncertain size and may include abuse of other agents, it is not always possible to reliably estimate their frequency or establish a causal relationship to drug exposure.

9.3 Dependence

Behaviors Associated with Addiction

Continued abuse of testosterone and other anabolic steroids, leading to addiction is characterized by the following behaviors:

- Taking greater dosages than prescribed
- Continued drug use despite medical and social problems due to drug use
- Spending significant time to obtain the drug when supplies of the drug are interrupted
- Giving a higher priority to drug use than other obligations
- Having difficulty in discontinuing the drug despite desires and attempts to do so
- Experiencing withdrawal symptoms upon abrupt discontinuation of use

Physical dependence is characterized by withdrawal symptoms after abrupt drug discontinuation or a significant dose reduction of a drug. Individuals taking supratherapeutic doses of testosterone may experience withdrawal symptoms lasting for weeks or months which include depressed mood, major depression, fatigue, craving, restlessness, irritability, anorexia, insomnia, decreased libido and hypogonadotropic hypogonadism.

Drug dependence in individuals using approved doses of testosterone for approved indications has not been documented.

10 OVERDOSAGE

There is a single report of acute overdosage after parenteral administration of an approved testosterone product in the literature. This subject had serum testosterone concentrations of up to 11,400 ng/dL, which were implicated in a cerebrovascular accident. There were no reports of overdose in the testosterone gel clinical trial.

Treatment of overdosage would consist of discontinuation of testosterone gel, washing the application site with soap and water, and appropriate symptomatic and supportive care.

11 DESCRIPTION

Testosterone Topical Gel is a clear, colorless, odorless, gel containing testosterone, USP. Testosterone Topical Gel is available in a metered-dose pump. Each pump actuation provides 10 mg of testosterone, USP and each container is capable of dispensing 120 pump actuations. One (1) pump actuation dispenses 0.5 g of gel.

The active pharmacologic ingredient in Testosterone Topical Gel is testosterone, USP. Testosterone, USP is a white to almost white powder described chemically as 17-beta hydroxyandrost-4-en-3-one.

Pharmacologically inactive ingredients in testosterone topical gel are: butylated hydroxytoluene, carbomer 1382, dehydrated alcohol, isopropyl alcohol, oleic acid, propylene glycol, purified water, and trolamine.

12 CLINICAL PHARMACOLOGY

12.1 Mechanism of Action

Endogenous androgens, including testosterone and dihydrotestosterone (DHT), are responsible for the normal growth and development of the male sex organs and for the maintenance of secondary sex characteristics. These effects include the growth and maturation of the prostate, seminal vesicles, penis, and scrotum; the development of male hair distribution, such as facial, pubic, chest, and axillary hair; laryngeal enlargement; vocal cord thickening; alterations in body musculature and fat distribution. Testosterone and DHT are necessary for the normal development of secondary sex characteristics.

Male hypogonadism, a clinical syndrome resulting from insufficient secretion of testosterone, has 2 main etiologies. Primary hypogonadism is caused by defects of the gonads, such as Klinefelter’s syndrome or Leydig cell aplasia, whereas secondary hypogonadism is the failure of the hypothalamus or pituitary to produce sufficient gonadotropins (FSH, LH).

12.2 Pharmacodynamics

No specific pharmacodynamic studies were conducted using testosterone gel.

12.3 Pharmacokinetics

Absorption
Testosterone gel delivers physiologic amounts of testosterone, producing serum testosterone concentrations that approximate normal concentrations (greater than 300 ng/dL) seen in healthy men.

Testosterone gel provides continuous transdermal delivery of testosterone for 24 hours following a single application to clean, dry, intact skin of the front and inner thighs (Figure 1).

Figure 1: Mean (±SD) Serum Total Testosterone Concentrations on Day 7 in Patients Following Testosterone Gel Once-Daily Application of 40 mg of Testosterone (N=12)

Distribution
Circulating testosterone is primarily bound in the serum to sex hormone-binding globulin (SHBG) and albumin. Approximately 40% of testosterone in plasma is bound to SHBG, 2% remains unbound (free) and the rest is loosely bound to albumin and other proteins.

Metabolism
Testosterone is metabolized to various 17-keto steroids through 2 different pathways. The major active metabolites of testosterone are estradiol and DHT.

Excretion
There is considerable variation in the half-life of testosterone concentration as reported in the literature, ranging from 10 to 100 minutes. About 90% of a dose of testosterone given intramuscularly is excreted in the urine as glucuronic acid and sulfuric acid conjugates of testosterone and its metabolites. About 6% is excreted in the feces, mostly in the unconjugated form. Inactivation of testosterone occurs primarily in the liver.

Potential for Testosterone Transfer
The potential for testosterone transfer from healthy males dosed with testosterone gel to healthy females was evaluated in a placebo-controlled, 3-way crossover study. The washout period was approximately 29 days. Six (6) males were treated with either testosterone gel (30 mg testosterone) or placebo to 1 thigh only. At 2 hours after the application of testosterone gel to males, the females rubbed their forearms for 15 minutes on the thigh of the males. Serum concentrations of testosterone were monitored in females for 24 hours after the transfer procedure. When direct skin-to-skin transfer occurred with testosterone gel mean average concentration (Cavg) increased by 134% and mean maximum concentration (Cmax) increased by 191%, compared to direct skin-to-skin transfer with placebo. When transfer occurred with testosterone gel while covering a thigh with boxer shorts, mean Cavg decreased by 3% and mean Cmax increased by 2%, compared to direct skin-to-skin transfer with placebo [see Dosage and Administration (2.2)].

Effect of Showering
In a 2-way crossover study, the effects of showering on the pharmacokinetics of total testosterone following application of testosterone gel (30 mg testosterone to each thigh; total 60 mg testosterone) were assessed in 7 hypogonadal males. There were two 7-day treatment phases, with showering 2 hours post testosterone gel application, and without showering on Day 7 of each treatment phase. Showering decreased Cavg by 3% and it increased Cmax by 13% [see Dosage and Administration (2.2)].

Effect of Hand Washing and Application Site (Inner Thigh) Washing
In an open-label, single-dose study, the amount of residual testosterone on the application finger and application site after washing was evaluated in 12 healthy male subjects. Prior to application of testosterone gel, each index finger and each intended application site (left and right front and inner thighs) was wiped using dry sponges to assess baseline skin testosterone. Subjects then used each index finger to rub testosterone gel (40 mg testosterone) onto each inner thigh. On one side, the index finger was immediately wiped using dry sponges to collect residual testosterone. On the other side, each subject washed their hands with liquid soap and warm tap water immediately after drug application, then wipe the index finger using dry sponges to collect residual testosterone. A mean (SD) of 0.002 (0.006) mg of residual testosterone (i.e., 99.8% reduction compared to when hand was not washed) was recovered after washing hands with liquid soap and warm tap water.

Two (2) hours after the application of testosterone gel onto each inner thigh, one thigh was wiped using dry sponges. On the other thigh, the application site was washed with liquid soap and warm tap water, dried, and then wiped using dry sponges. The sponges were assayed for testosterone. A mean (SD) of 0.24 (0.009) mg of residual testosterone (i.e., 94.3% reduction compared to when application site was not washed) was recovered after application site washing.

13 NONCLINICAL TOXICOLOGY

13.1 Carcinogenesis, Mutagenesis, Impairment of Fertility

Carcinogenesis

Testosterone has been tested by subcutaneous injection and implantation in mice and rats. In mice, implant-induced cervical-uterine tumors metastasized in some cases. There is suggestive evidence that injection of testosterone into some strains of female mice increases their susceptibility to hepatoma. Testosterone is also known to increase the number of tumors and decrease the degree of differentiation of chemically induced carcinomas of the liver in rats.

Mutagenesis

Testosterone was negative in the in vitro Ames and in the in vivo mouse micronucleus assays.

Impairment of Fertility

The administration of exogenous testosterone has been reported to suppress spermatogenesis in the rat, dog, and non-human primates, which was reversible on cessation of the treatment.

14 CLINICAL STUDIES

14.1 Clinical Study in Hypogonadal Males

Testosterone gel was evaluated in a multicenter, 90-day open-label, non-comparative trial of 149 hypogonadal males with body mass index (BMI) greater than or equal to 22 kg/m^2 and less than 35 kg/m^2 and 18 to 75 years of age (mean age 54.5 years). The patients were screened for a single serum total testosterone concentration less than 250 ng/dL, or 2 consecutive serum total testosterone concentrations less than 300 ng/dL. Patients were caucasian (80.5%), black (10.1%), hispanic (7.4%), and other (2.0%).

Testosterone gel was applied once each morning to the thighs at a starting dose of 40 mg of testosterone (4 pump actuations) per day. The dose was adjusted between a minimum of 10 mg and a maximum of 70 mg testosterone on the basis of total serum testosterone concentration obtained 2 hours post testosterone gel application on Days 14, 35, and 60 (± 3 days).

The primary endpoint was the percentage of patients with Cavg within the normal range (greater than or equal to 300 ng/dL and less than or equal to 1140 ng/dL) on Day 90. In patients treated with testosterone gel, 77.5% (100/129) had Cavg within the normal range on Day 90. The secondary endpoint was the percentage of patients with Cmax above 3 pre-determined limits. The percentages of patients with Cmax greater than 1500 ng/dL, and between 1800 and 2499 ng/dL on Day 90 were 5.4% and 1.6%, respectively. No patient had a Cmax greater than or equal to 2500 ng/dL on Day 90.

Dose titrations on Days 14, 35, and 60 resulted in mean (SD) Cavg and Cmax for final doses of 10 mg to 70 mg on Day 90 shown in Table 5.

Table 5: Mean (±SD) Steady-State Testosterone Concentrations (Cavg and Cmax) by Final Dose on Day 90
 |  | Final Dose
 |  | 10mg (n=1) | 20mg (n=6) | 30mg (n=16) | 40mg (n=30) | 50mg (n=26) | 60mg (n=27) | 70mg (n=23)
Cavg (ng/dL) | Mean | 196 | 464 | 392 | 444 | 483 | 441 | 415
Cavg (ng/dL) | SD |  | 205 | 164 | 176 | 156 | 163 | 136
Cmax (ng/dL) | Mean | 503 | 971 | 775 | 855 | 964 | 766 | 724
Cmax (ng/dL) | SD |  | 399 | 278 | 417 | 389 | 292 | 313

Figure 2 summarizes the pharmacokinetic profiles of total testosterone in patients completing 90 days of testosterone gel treatment administered as 40 mg of testosterone once-daily for the initial 14 days followed by possible titration according to follow-up testosterone measurements.

Figure 2: Mean (±SD) Steady-State Serum Total Testosterone Concentrations on Day 90 (N=129)

Additionally, there were no clinically significant changes from baseline for SHBG (slight decrease), estradiol (slight increase), and ratio of DHT to total testosterone (slight increase) at Day 90.

16 HOW SUPPLIED/STORAGE AND HANDLING

Testosterone Topical Gel is supplied in 60 g canisters with a metered dose pump that delivers 10 mg of testosterone, USP per complete pump actuation. The metered dose pump is capable of dispensing 120 metered pump actuations. One (1) pump actuation dispenses 0.5 g of gel.

Testosterone Topical Gel is available in packages of 1 canister (NDC 0591-2363-60).

Store at 20o to 25oC (68o to 77oF) [See USP Controlled Room Temperature]. Do Not Freeze.

Used Testosterone Topical Gel canisters should be discarded in household trash in a manner that prevents accidental application or ingestion by children or pets.

17 PATIENT COUNSELING INFORMATION

See FDA-approved Medication Guide.

Patients should be informed of the following information:

17.1 Use in Men with Known or Suspected Prostate or Breast Cancer

Men with known or suspected prostate or breast cancer should not use testosterone gel [see Contraindications (4) and Warnings and Precautions (5.1)].

17.2 Potential for Secondary Exposure to Testosterone and Steps to Prevent Secondary Exposure

Secondary exposure to testosterone in children and women can occur with the use of testosterone gel in men. Cases of secondary exposure to testosterone in children have been reported.

Physicians should advise patients of the reported signs and symptoms of secondary exposure which may include the following:

- In children; unexpected sexual development including inappropriate enlargement of the penis or clitoris, premature development of pubic hair, increased erections, and aggressive behavior.
- In women; changes in hair distribution, increase in acne, or other signs of testosterone effects.
- The possibility of secondary exposure to testosterone gel should be brought to the attention of a healthcare provider.
- Testosterone gel should be promptly discontinued until the cause of virilization is identified.

Strict adherence to the following precautions is advised to minimize the potential for secondary exposure to testosterone from testosterone gel in men [see Medication Guide]:

- Children and women should avoid contact with unwashed or unclothed application site(s) of men using testosterone gel.
- Patients using testosterone gel should apply the product as directed and strictly adhere to the following:

- Wash hands with soap and water after application.
- Cover the application site(s) with clothing after the gel has dried.
- Wash the application site(s) thoroughly with soap and water prior to any situation where skin-to-skin contact of the application site with another person is anticipated.
- In the event that unwashed or unclothed skin to which testosterone gel has been applied comes in contact with the skin of another person, the general area of contact on the other person should be washed with soap and water as soon as possible [see Dosage and Administration (2.2), Warnings and Precautions (5.2), and Clinical Pharmacology (12.3)].

17.3 Potential Adverse Reactions with Androgens

Patients should be informed that treatment with androgens may lead to adverse reactions which include:

- Changes in urinary habits such as increased urination at night, trouble starting your urine stream, passing urine many times during the day, having an urge that you have to go to the bathroom right away, having a urine accident, being unable to pass urine, and weak urine flow.
- Breathing disturbances, including those associated with sleep, or excessive daytime sleepiness.
- Too frequent or persistent erections of the penis.
- Nausea, vomiting, changes in skin color, or ankle swelling.

17.4 Patients Should Be Advised of the Following Instructions for Use

- Read the Medication Guide before starting testosterone gel therapy and reread it each time the prescription is renewed.
- Testosterone gel should be applied and used appropriately to maximize the benefits and to minimize the risk of secondary exposure in children and women.
- Keep testosterone gel out of the reach of children.
- Testosterone gel is an alcohol based product and is flammable; therefore avoid fire, flame, or smoking until the gel has dried.
- It is important to adhere to all recommended monitoring.
- Report any changes in their state of health, such as changes in urinary habits, breathing, sleep, and mood.
- Testosterone gel is prescribed to meet the patient’s specific needs, therefore, the patient should never share testosterone gel with anyone.
- Wait 2 hours before swimming or washing following application of testosterone gel. This will ensure that the greatest amount of testosterone gel is absorbed into their system.

Manufactured by:
Actavis Laboratories UT, Inc.
Salt Lake City, UT 84108 USA

Distributed by:
Actavis Pharma, Inc.
Parsippany, NJ 07054 USA

Rev. B 6/2020

MEDICATION GUIDE

Testosterone (tes tos' ter one) CIII
Topical Gel

What is the most important information I should know about testosterone gel?

1. Testosterone gel can transfer from your body to others including, children and women. Children and women should avoid contact with the unwashed or not covered (unclothed) areas where testosterone gel has been applied to your skin. Early signs and symptoms of puberty have occurred in young children who have come in direct contact with testosterone by touching areas where men have used testosterone gel.

Children

Signs and symptoms of early puberty in a child when they come in direct contact with testosterone gel may include:

Abnormal sexual changes:

- enlarged penis or clitoris.
- early growth of hair near the vagina or around the penis (pubic hair).
- erections or acting out sexual urges (sex drive).

Behavior problems:

- acting aggressively, behaving in an angry or violent way.
  Women
  Signs and symptoms in women when they come in direct contact with testosterone gel may
  include:
- changes in body hair.
- an abnormal increase in pimples (acne).

Stop using testosterone gel and call your healthcare provider right away if you see any signs and

symptoms in a child or a woman that may have happened through accidental touching of the area where you have applied testosterone gel.

2. To lower the risk of transfer of testosterone gel from your body to others, follow these

important instructions:

- Apply testosterone gel only to the front and inside area of your thighs that will be covered by clothing.
- Wash your hands right away with soap and water after applying testosterone gel.
- After the gel has dried, cover the application area with clothing. Keep the area covered until you have washed the application area well or have showered.
- If you expect to have skin-to-skin contact with another person, first wash the application area well with soap and water.
- If a child or woman touches the area where you have applied testosterone gel, that area on the child or woman should be washed well with soap and water right away.

What is testosterone gel?

Testosterone gel is a prescription medicine that contains testosterone. Testosterone gel is used to treat adult males who have low or no testosterone due to certain medical conditions.

- Your healthcare provider will test your blood before you start and while you are using testosterone gel.
- It is not known if testosterone gel is safe or effective to treat men who have low testosterone due to aging.
- It is not known if testosterone gel is safe or effective in children younger than 18 years old. Improper use of testosterone gel may affect bone growth in children.

Testosterone gel is a controlled substance (CIII) because it contains testosterone that can be a target for people who abuse prescription medicines. Keep your testosterone gel in a safe place to protect it. Never give testosterone gel to anyone else, even if they have the same symptoms you have. Selling or giving away this medicine may harm others and is against the law.

Testosterone gel is not meant for use in women.

Do not use testosterone gel if you:

- have breast cancer.
- have or might have prostate cancer.
- are pregnant. Testosterone gel may harm your unborn baby.
- Women who are pregnant should avoid contact with the area of skin where testosterone gel has been applied.

Before using testosterone gel, tell your healthcare provider about all of your medical conditions

including if you:

- have breast cancer.
- have or might have prostate cancer.
- have urinary problems due to an enlarged prostate.
- have heart problems.
- have liver or kidney problems.
- have problems breathing while you sleep (sleep apnea).

Tell your healthcare provider about all the medicines you take, including prescription and over-the-counter

medicines, vitamins, and herbal supplements.

Using testosterone gel with certain other medicines can affect each other. Especially, tell your healthcare

provider if you take:

- insulin
- medicines that decrease blood clotting (blood thinners)
- corticosteroids

How should I use testosterone gel?

- See the detailed Instructions for Use for information about how to use testosterone gel at the end of this Medication Guide.
- It is important that you apply testosterone gel exactly as your healthcare provider tells you to.
- Your healthcare provider may change your testosterone gel dose. Do not change your testosterone gel dose without talking to your healthcare provider.
- Apply testosterone gel in the morning. If you shower or bathe, testosterone gel should be applied afterwards.

What are the possible side effects of testosterone gel?

Testosterone gel can cause serious side effects including:

See “What is the most important information I should know about testosterone gel?”

- If you already have enlargement of your prostate gland your signs and symptoms can get worse while using testosterone gel. This can include:
  - increased urination at night.
  - trouble starting your urine stream.
  - having to pass urine many times during the day.
  - having an urge to go to the bathroom right away.
  - having a urine accident.
  - being unable to pass urine or weak urine flow.
- Possible increased risk of prostate cancer. Your healthcare provider should check you for prostate cancer or any other prostate problems before you start and while you use testosterone gel.
- Blood clots in the legs or lungs. Signs and symptoms of a blood clot in your leg can include leg pain, swelling or redness. Signs and symptoms of a blood clot in your lungs can include difficulty breathing or chest pain.
- Possible increased risk of heart attack or stroke.
- In large doses testosterone gel may lower your sperm count.
- Swelling of your ankles, feet, or body, with or without heart failure.
- Enlarged or painful breasts.
- Have problems breathing while you sleep (sleep apnea).
- Increased red blood cell count.

Call your healthcare provider right away if you have any of the serious side effects listed above.

The most common side effects of testosterone gel include:

- skin redness or irritation where testosterone gel is applied
- increased in blood level of Prostate Specific Antigen (a test used to screen for prostate cancer)
- abnormal dreams

Other side effects include more erections than are normal for you or erections that last a long time.

Tell your healthcare provider if you have any side effect that bothers you or that does not go away.

These are not all the possible side effects of testosterone gel. For more information, ask your healthcare provider or pharmacist.

Call your doctor for medical advice about side effects. You may report side effects to FDA at 1-800-

FDA-1088.

How should I store testosterone gel?

- Store testosterone gel at room temperature between 68º to 77ºF (20º to 25ºC).
- When it is time to throw away the canister, safely throw away used testosterone gel in household trash. Be careful to prevent accidental exposure of children or pets.
- Keep testosterone gel away from fire.
- Do not freeze testosterone gel.

Keep testosterone gel and all medicines out of the reach of children.

General information about testosterone gel

Medicines are sometimes prescribed for purposes other than those listed in a Medication Guide. Do not use testosterone gel for a condition for which it was not prescribed. Do not give testosterone gel to other people, even if they have the same symptoms you have. It may harm them.

You can ask your pharmacist or healthcare provider for information about testosterone gel that is written for health professionals.

What are the ingredients in testosterone gel?

Active ingredients: testosterone

Inactive ingredients: butylated hydroxytoluene, carbomer 1382, dehydrated alcohol, isopropyl alcohol, oleic acid, propylene glycol, purified water, and trolamine.

Manufactured by: Actavis Laboratories UT, Inc., Salt Lake City, UT 84108 USA

Distributed by: Actavis Pharma, Inc., Parsippany, NJ 07054 USA

For more information about testosterone gel, call 1-888-838-2872.

This Medication Guide has been approved by the U.S. Food and Drug Administration. Revised: C 6/2020

INSTRUCTIONS FOR USE

Testosterone (tes tos' ter one) CIII
Topical Gel

Read this Instructions for Use for testosterone gel before you start using it and each time you get a refill. There may be new information. This leaflet does not take the place of talking to your healthcare provider about your medical condition or treatment.

Applying testosterone gel:

- Apply testosterone gel only to areas that will be covered by shorts or pants.
- Testosterone gel should be applied to the front and inner part of your thighs only. Do not apply testosterone gel to the area of the thigh closest to the scrotum. Do not apply testosterone gel to any other parts of your body such as your stomach area (abdomen), penis, scrotum, shoulders or upper arms.
- Apply testosterone gel in the morning. If you shower or bathe, testosterone gel should be applied afterwards.
- Avoid swimming, showering, or bathing for at least 2 hours after you apply testosterone gel.
- Testosterone gel is flammable until dry. Let testosterone gel dry before smoking or going near an open flame.
- Wash your hands with soap and water right after you apply testosterone gel.
- Before using a new canister of testosterone gel for the first time, you will need to prime the pump. To prime the testosterone gel pump, gently push down on the pump 8 times. Do not use any testosterone gel that comes out while priming. Wash it down the sink or throw it in the trash to avoid accidental exposure to others. Your testosterone gel pump is now ready to use.
- Use testosterone gel exactly as your healthcare provider tells you to use it. Your healthcare provider will tell you the dose of testosterone gel that is right for you.
- Press down on the pump to apply the medicine directly on clean, dry, skin that is not broken on the front and inner part of your thighs. Use 1 finger to gently rub testosterone gel evenly onto the front and inner part of each thigh.

- Let the application site dry completely before putting on shorts or pants.
- Wash your hands right away with soap and water.

How should I store testosterone gel?

- Store testosterone gel at room temperature between 68º to 77ºF (20ºC to 25ºC).
- When it is time to throw away the canister, safely throw away used testosterone gel in the household trash. Be careful to prevent accidental exposure of children or pets.
- Keep testosterone gel away from fire.
- Do not freeze testosterone gel.

Keep testosterone gel and all medicines out of the reach of children.

This Instructions for Use has been approved by the U.S. Food and Drug Administration.

Manufactured by:

Actavis Laboratories UT, Inc.

Salt Lake City, UT 84108 USA

Distributed by:

Actavis Pharma, Inc.

Parsippany, NJ 07054 USA

Rev. B 6/2020

PACKAGE LABEL PRINCIPAL DISPLAY PANEL

NDC 0591-2363-60
For External Use Only
Testosterone Topical Gel CIII
10 mg of testosterone per pump actuation*
60 g
Alcohol 18.2% v/v
*Each actuation delivers 0.5 g of gel.
Multi-dose pump capable of dispensing 120 metered pump actuations.
Rx Only
1 canister containing 60 grams